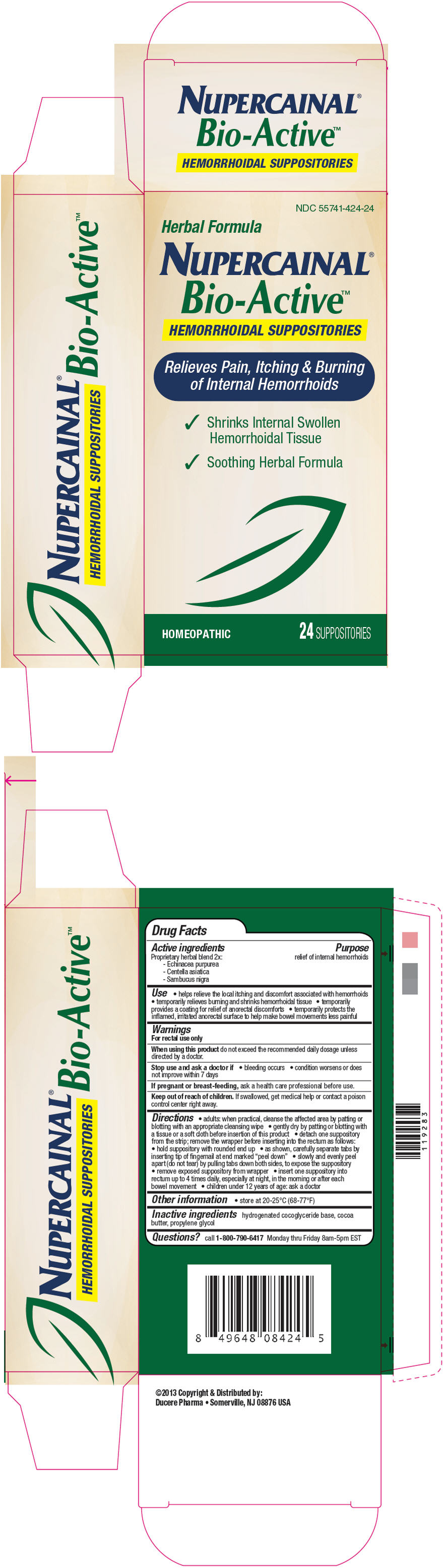 DRUG LABEL: Nupercainal Bio-Active Hemorrhoidal
NDC: 55741-424 | Form: SUPPOSITORY
Manufacturer: Ducere Pharma
Category: homeopathic | Type: HUMAN OTC DRUG LABEL
Date: 20140425

ACTIVE INGREDIENTS: Echinacea purpurea 0.1 g/1 1; Centella asiatica 0.1 g/1 1; Sambucus nigra flowering top 0.1 g/1 1
INACTIVE INGREDIENTS: hydrogenated coco-glycerides; cocoa butter; propylene glycol

Nupercainal® Bio-Active™ Hemorrhoidal Suppositories

Drug Facts

Active ingredients

Proprietary herbal blend 2x:
- Echinacea purpurea
- Centella asiatica
- Sambucus nigra

Purpose

relief of internal hemorrhoids

Use

- helps relieve the local itching and discomfort associated with hemorrhoids
- temporarily relieves burning and shrinks hemorrhoidal tissue
- temporarily provides a coating for relief of anorectal discomforts
- temporarily protects the inflamed, irritated anorectal surface to help make bowel movements less painful

Warnings

For rectal use only

When using this product do not exceed the recommended daily dosage unless directed by a doctor.

Stop use and ask a doctor if

- bleeding occurs
- condition worsens or does not improve within 7 days

PREGNANCY OR BREAST FEEDING

If pregnant or breast-feeding, ask a health care professional before use.

Keep out of reach of children. If swallowed, get medical help or contact a poison control center right away.

Directions

- adults: when practical, cleanse the affected area by patting or blotting with an appropriate cleansing wipe
- gently dry by patting or blotting with a tissue or a soft cloth before insertion of this product
- detach one suppository from the strip; remove the wrapper before inserting into the rectum as follows:
  - hold suppository with rounded end up
  - as shown, carefully separate tabs by inserting tip of fingernail at end marked "peel down"
  - slowly and evenly peel apart (do not tear) by pulling tabs down both sides, to expose the suppository
  - remove exposed suppository from wrapper
  - insert one suppository into rectum up to 4 times daily, especially at night, in the morning or after each bowel movement
- children under 12 years of age: ask a doctor

Other information

- store at 20-25°C (68-77°F)

Inactive ingredients

hydrogenated cocoglyceride base, cocoa butter, propylene glycol

Questions?

call 1-800-790-6417 Monday thru Friday 8am-5pm EST

Distributed by:
Ducere Pharma • Somerville, NJ 08876 USA

PRINCIPAL DISPLAY PANEL - 24 Suppository Carton

NDC 55741-424-24

Herbal Formula

NUPERCAINAL®
Bio-Active™
HEMORRHOIDAL SUPPOSITORIES

Relieves Pain, Itching & Burning
of Internal Hemorrhoids

✔ Shrinks Internal Swollen
  Hemorrhoidal Tissue
✔ Soothing Herbal Formula

HOMEOPATHIC
24 SUPPOSITORIES